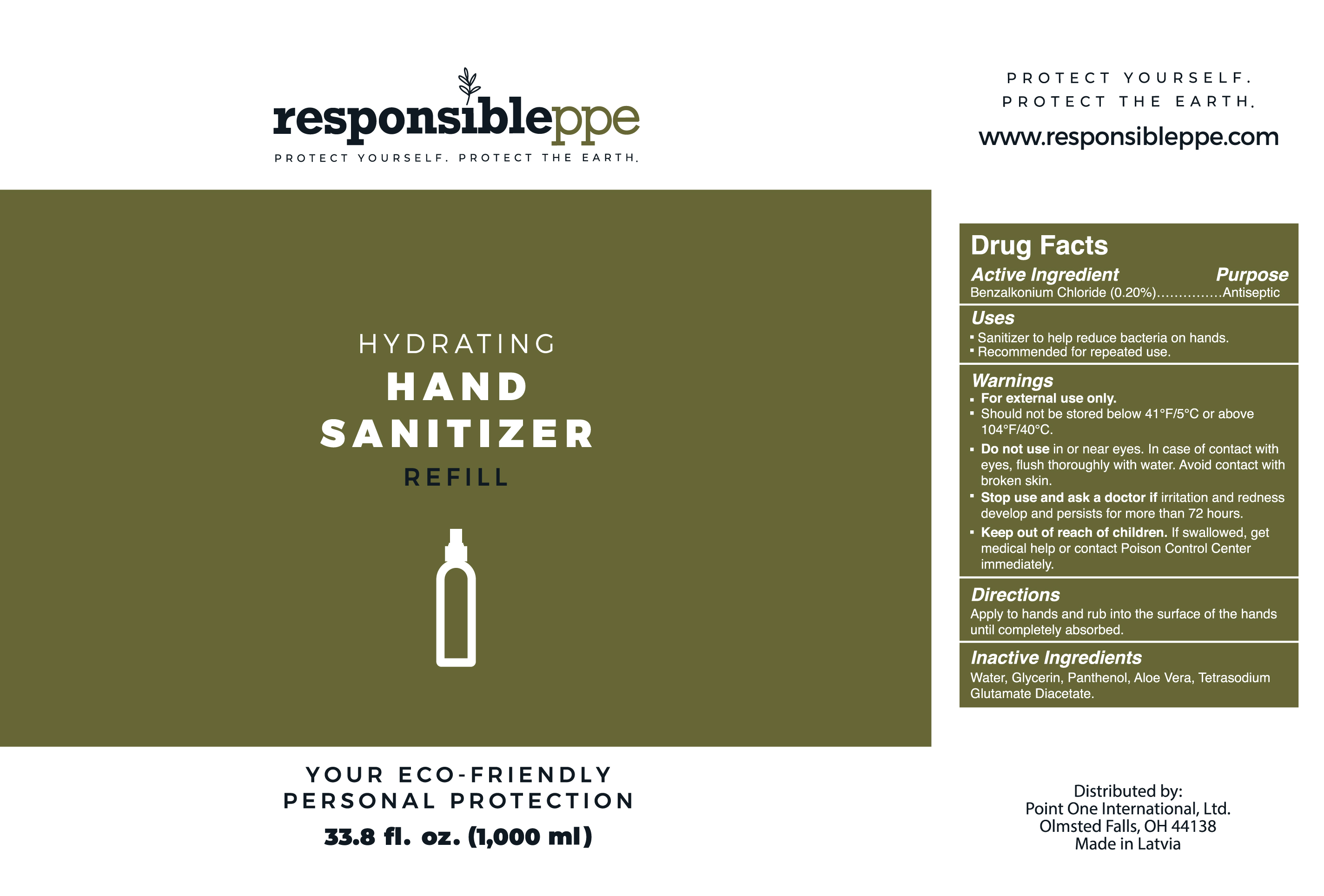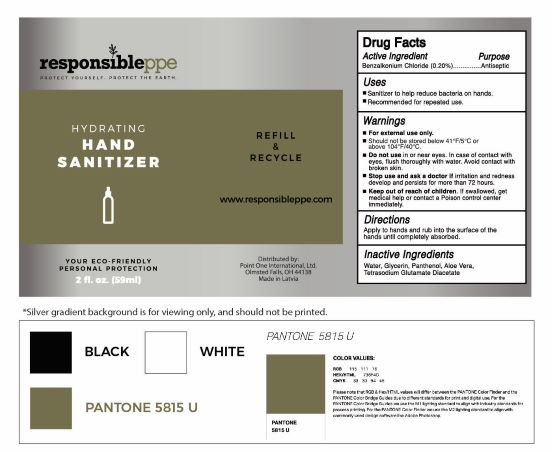 DRUG LABEL: Hand Sanitizer
NDC: 78522-104 | Form: LIQUID
Manufacturer: Northmed SIA
Category: otc | Type: HUMAN OTC DRUG LABEL
Date: 20211026

ACTIVE INGREDIENTS: BENZALKONIUM CHLORIDE 2 mg/59 mL
INACTIVE INGREDIENTS: TETRASODIUM GLUTAMATE DIACETATE; ALOE VERA LEAF; PANTHENOL; GLYCERIN; WATER

ACTIVE INGREDIENT

Benzalkonium Chloride (.20%). Purpose: Antiseptic

PURPOSE

Antiseptic. Hand Sanitizer.

INDICATIONS AND USAGE

Sanitizer to help reduce bacteria on hands. Recommended for repeated use.

WARNINGS

For external use only.

STORAGE AND HANDLING

Should not be sotred below 41F/5C or above 104F/40C.

Do not use in or near eyes. In case of contact with eyes, flush thoroughly with water. Avoid contact with broken skin.

Stop use and ask a doctor if irritation and rendess develop and persists for more than 72 hours.

Keep out of reach of children. If swallowed, get medical help or contact a Poison control center immediately.

DOSAGE AND ADMINISTRATION

Apply to hands and rub into the surface of the hands until completely absorbed.

INACTIVE INGREDIENT

Water, Glycerin, Panthenol, Aloe Vera, Tetrasodium Glutamate Diacetate.

PACKAGE LABEL

1000 mL (33.8 fl. oz.) NDC: 78522-104-00

2 fl. oz. 59ml. NDC: 78522-100-00